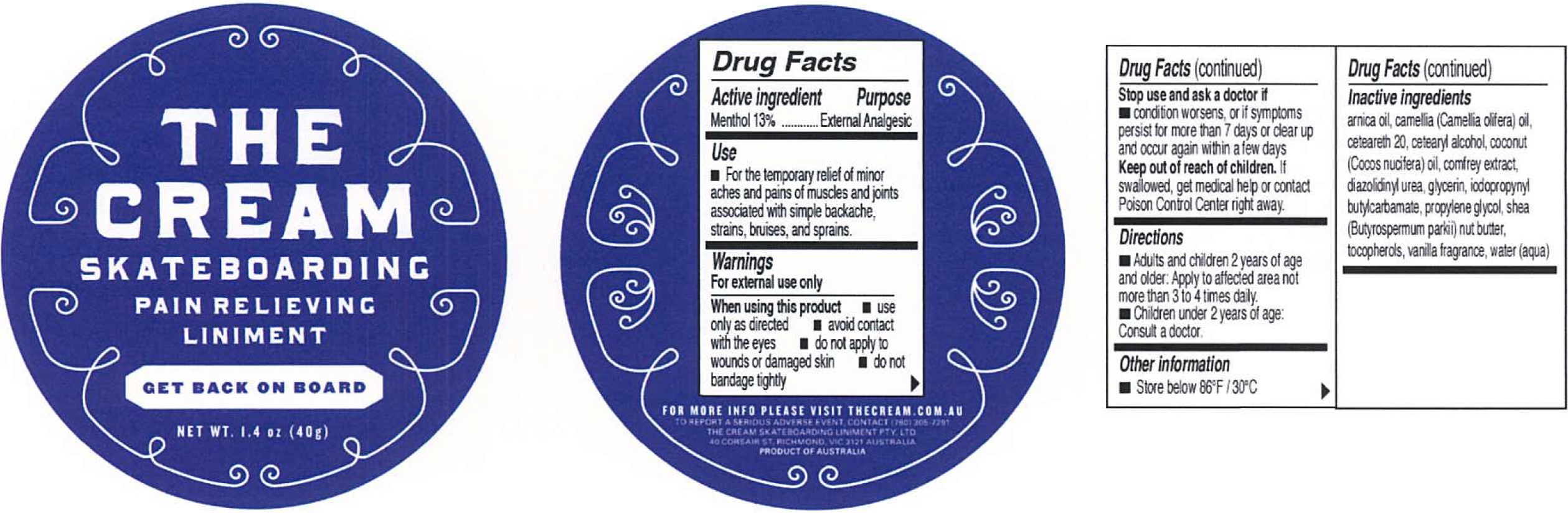 DRUG LABEL: The Skateboarding Pain Relieving Liniment
NDC: 72045-000 | Form: CREAM
Manufacturer: The Cream Skateboarding Liniment Pty Ltd
Category: otc | Type: HUMAN OTC DRUG LABEL
Date: 20180130

ACTIVE INGREDIENTS: MENTHOL 130 mg/1 g
INACTIVE INGREDIENTS: CAMELLIA OIL; POLYOXYL 20 CETOSTEARYL ETHER; CETOSTEARYL ALCOHOL; COCONUT OIL; DIAZOLIDINYL UREA; GLYCERIN; IODOPROPYNYL BUTYLCARBAMATE; PROPYLENE GLYCOL; TOCOPHEROL; WATER

The Cream Skateboarding Pain Relieving Liniment

Active ingredient

Menthol 13%

Purpose

External Analgesic

Use

- For the temporary relief of minor aches and pains of muscles and joints associated with simple backache, strains, bruises, and sprains.

Warnings

For external use only

When using this product

- use only as directed
- avoid contact with the eyes
- do not apply to wounds or dmaged skin
- do not bandage tightly

Stop use and ask a doctor if

- condition worsens, or if symptoms persist for more than 7 days or clear up and occur again within a few days

Keep out of reach of children.

If swallowed, get medical help or contact Poison Control Center right away.

Directions

- Adults and children 2 years of age and older: Apply to affected area not more than 3 to 4 times daily.
- Children under 2 years of age: Consult a doctor.

Other information

- Store below 86°F / 30°C

Inactive ingredients

arnica oil, camellia (Camellia olifera) oil, ceteareth 20, cetearyl alcohol, coconut (Cocos nucifera) oil, comfrey extract, diazolidinyl urea, glycerin, iodopropynyl butylcarbamate, propylene glycol, shea (Butyrospermum parkii) nut butter, tocopherols, vanilla fragrance, water (aqua)